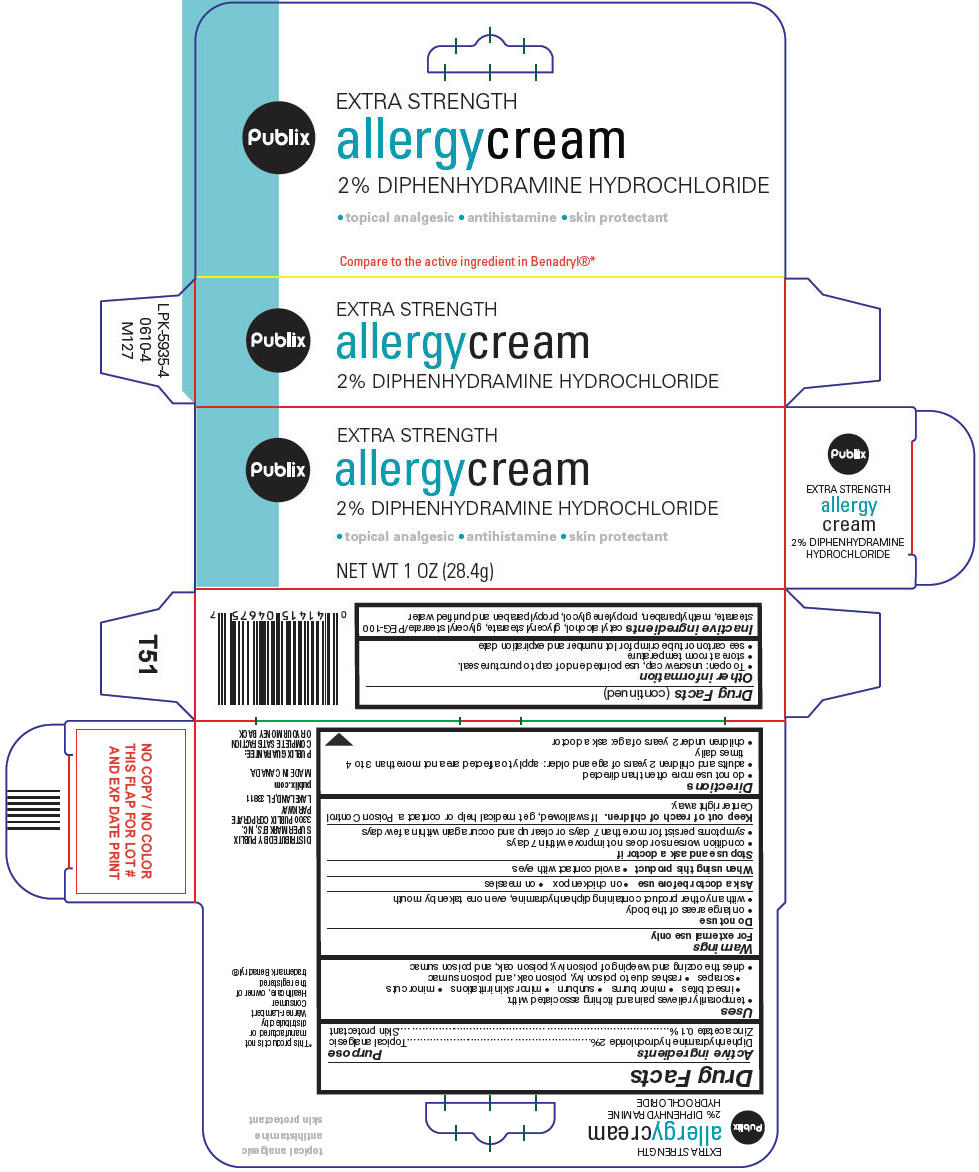 DRUG LABEL: Publix 
NDC: 41415-046 | Form: CREAM
Manufacturer: Publix Super Markets Inc
Category: otc | Type: HUMAN OTC DRUG LABEL
Date: 20190227

ACTIVE INGREDIENTS: diphenhydramine hydrochloride 20 mg/1 g; zinc acetate 1 mg/1 g
INACTIVE INGREDIENTS: cetyl alcohol; glyceryl monostearate; PEG-100 stearate; methylparaben; propylene glycol; propylparaben; water

Publix
allergy cream

Drug Facts

ACTIVE INGREDIENT

Active ingredients | Purpose
Diphenhydramine hydrochloride 2% | Topical analgesic
Zinc acetate 0.1% | Skin protectant

Uses

- temporarily relieves pain and itching associated with:
  - insect bites
  - minor burns
  - sunburn
  - minor skin irritations
  - minor cuts
  - scrapes
  - rashes due to poison ivy, poison oak, and poison sumac
- dries the oozing and weeping of poison ivy, poison oak, and poison sumac

Warnings

For external use only

Do not use

- on large areas of the body
- with any other product containing diphenhydramine, even one taken by mouth

Ask a doctor before use

- on chicken pox
- on measles

When using this product

- avoid contact with eyes

Stop use and ask a doctor if

- condition worsens or does not improve within 7 days
- symptoms persist for more than 7 days or clear up and occur again within a few days

Keep out of reach of children. If swallowed, get medical help or contact a Poison Control Center right away.

Directions

- do not use more often than directed
- adults and children 2 years of age and older: apply to affected area not more than 3 to 4 times daily
- children under 2 years of age: ask a doctor

Other information

- To open: unscrew cap, use pointed end of cap to puncture seal.
- store at room temperature
- see carton or tube crimp for lot number and expiration date

Inactive ingredients

cetyl alcohol, glyceryl stearate, glyceryl stearate/PEG-100 stearate, methylparaben, propylene glycol, propylparaben and purified water

DISTRIBUTED BY PUBLIX SUPER MARKETS, INC.
3300 PUBLIX CORPORATE PARKWAY
LAKELAND, FL 33811

PRINCIPAL DISPLAY PANEL - 28.4g Tube Carton

EXTRA STRENGTH

Publix

allergycream

2% DIPHENHYDRAMINE HYDROCHLORIDE

• topical analgesic • antihistamine • skin protectant

NET WT 1 OZ (28.4g)